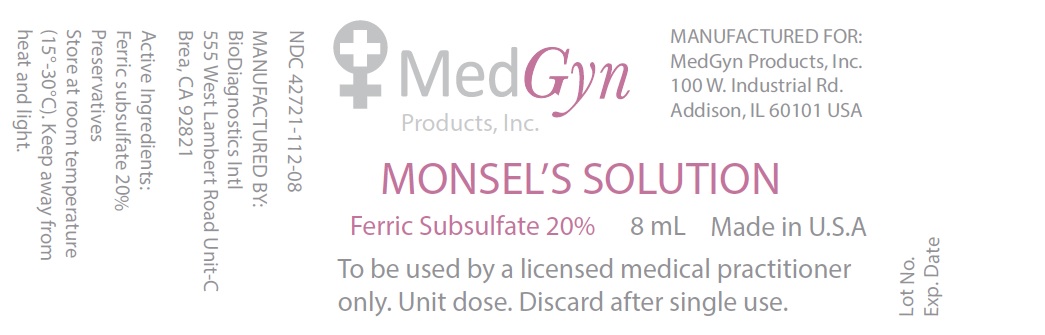 DRUG LABEL: Monsels Solution
NDC: 70880-112 | Form: SOLUTION
Manufacturer: MedGyn Products, Inc.
Category: prescription | Type: HUMAN PRESCRIPTION DRUG LABEL
Date: 20160729

ACTIVE INGREDIENTS: FERRIC SUBSULFATE 20 g/100 mL
INACTIVE INGREDIENTS: WATER

Monsel's Solution

DESCRIPTION

Ferric Subsulfate 20%

STORAGE AND HANDLING

Store at room temperature(15°-30°C). Keep away from heat and light.

INDICATIONS AND USAGE

Hemostasis of small cuts and biopsies

PRECAUTIONS

To be used by a licensed medical practitioner only. Unit dose. Discard after single use.

MANUFACTURED FOR:

MedGyn Products, Inc

100 W. Industrial Rd.

Addison,IL 60101 USA